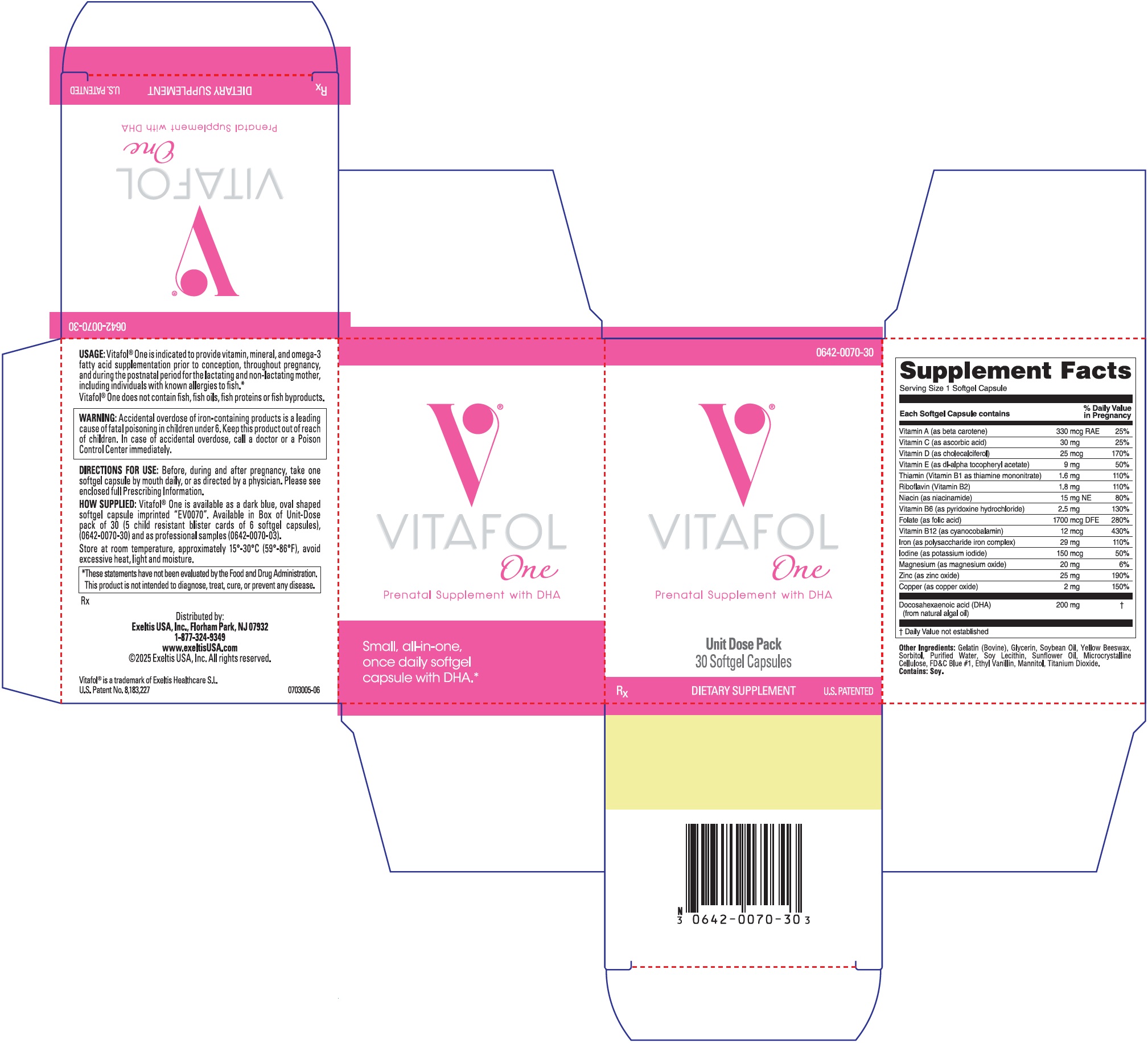 DRUG LABEL: Vitafol
NDC: 0642-0070 | Form: CAPSULE, GELATIN COATED
Manufacturer: Exeltis USA, Inc.
Category: prescription | Type: HUMAN PRESCRIPTION DRUG LABEL
Date: 20250320

ACTIVE INGREDIENTS: VITAMIN A 330 ug/1 1; ASCORBIC ACID 30 mg/1 1; THIAMINE MONONITRATE 1.6 mg/1 1; RIBOFLAVIN 1.8 mg/1 1; NIACIN 15 mg/1 1; PYRIDOXINE HYDROCHLORIDE 2.5 mg/1 1; CYANOCOBALAMIN 0.012 mg/1 1; FOLIC ACID 1700 ug/1 1; IODINE 0.15 mg/1 1; MAGNESIUM 20 mg/1 1; ZINC 25 mg/1 1; COPPER 2 mg/1 1; VITAMIN D 25 ug/1 1; OMEGA-3 FATTY ACIDS 200 mg/1 1; .ALPHA.-TOCOPHEROL 9 mg/1 1; IRON 29 mg/1 1
INACTIVE INGREDIENTS: SORBITOL; GLYCERIN; SOYBEAN OIL; WATER; YELLOW WAX; LECITHIN, SOYBEAN; TITANIUM DIOXIDE; GELATIN, UNSPECIFIED; SUNFLOWER OIL; FD&C BLUE NO. 1; ETHYL VANILLIN; MICROCRYSTALLINE CELLULOSE; MANNITOL

V®
Vitafol-One
Prenatal Supplement with DHA

Vitafol One®
Prenatal Supplement with DHA
Rx

COMPOSITION:

Each Softgel Capsule Contains:
VITAMINS AND MINERALS:
Vitamin A (as beta carotene) | 330 mcg RAE
Vitamin C (as ascorbic acid) | 30 mg
Vitamin D (as cholecalciferol) | 25 mcg
Vitamin E (as dl-alpha tocopheryl acetate) | 9 mg
Thiamin (Vitamin B1 as thiamine mononitrate) | 1.6 mg
Riboflavin (Vitamin B2) | 1.8 mg
Niacin (as niacinamide) | 15 mg NE
Vitamin B6 (as pyridoxine hydrochloride) | 2.5 mg
Folate (as folic acid) | 1700 mcg DFE
Vitamin B12 (as cyanocobalamin) | 12 mcg
Iron (as polysaccharide iron complex) | 29 mg
Iodine (as potassium iodide) | 150 mcg
Magnesium (as magnesium oxide) | 20 mg
Zinc (as zinc oxide) | 25 mg
Copper (as copper oxide) | 2 mg
Docosahexaenoic acid (DHA); (from natural algal oil) | 200 mg

Other Ingredients: Gelatin (Bovine), Glycerin, Soybean Oil, Yellow Beeswax, Sorbitol, Purified Water, Soy Lecithin, Sunflower Oil, Microcrystalline Cellulose, FD&C Blue #1, Ethyl Vanillin, Mannitol, Titanium Dioxide.

Contains: Soy.

USAGE:

Vitafol® One is indicated to provide vitamin, mineral, and omega-3 fatty acid supplementation prior to conception, throughout pregnancy, and during the postnatal period for the lactating and non-lactating mother, including individuals with known allergies to fish.*

CONTRAINDICATIONS:

Vitafol® One is contraindicated in patients with hypersensitivity to any of its components or color additives.

Folic acid is contraindicated in patients with untreated and uncomplicated pernicious anemia, and in those with anaphylactic sensitivity to folic acid.

Iron therapy is contraindicated in patients with hemochromatosis and patients with iron storage disease or the potential for iron storage disease due to chronic hemolytic anemia (e.g., inherited anomalies of hemoglobin structure or synthesis and/or red cell enzyme deficiencies, etc.), pyridoxine responsive anemia, or cirrhosis of the liver.

Cyanocobalamin is contraindicated in patients with sensitivity to cobalt or to cyanocobalamin (vitamin B-12).

WARNING:

Accidental overdose of iron-containing products is a leading cause of fatal poisoning in children under 6. Keep this product out of reach of children. In case of accidental overdose, call a doctor or a Poison Control Center immediately.

WARNINGS/PRECAUTIONS:

Vitafol® One should be used with caution in patients with known sensitivity or allergy to soy.

Vitamin D supplementation should be used with caution in those with hypercalcemia or conditions that may lead to hypercalcemia such as hyperparathyroidism and those who form calcium-containing kidney stones. High doses of vitamin D can lead to elevated levels of calcium that reside in the blood and soft tissues. Bone pain, high blood pressure, formation of kidney stones, renal failure, and increased risk of heart disease can occur.

Iodine should be used with caution in patients with an overactive thyroid.

Prolonged use of iron salts may produce iron storage disease. Folic acid, especially in doses above 0.1 mg daily, may obscure pernicious anemia, in that hematologic remission may occur while neurological manifestations remain progressive.

The use of folic acid doses above 1 mg daily may precipitate or exacerbate the neurological damage of vitamin B12 deficiency.

Consumption of more than 3 grams of omega-3 fatty acids per day from all sources may lead to excessive bleeding. Supplemental intake of omega-3 fatty acids such as DHA exceeding 2 grams per day is not recommended.

Avoid Overdosage. Keep out of the reach of children.

Drug Interactions:

Medications for an overactive thyroid (anti-thyroid drugs) used in conjunction with iodine supplementation may lead to hypothyroidism.

Medications for hypertension used in conjunction with iodine supplementation may increase potassium.

High doses of folic acid may result in decreased serum levels of the anticonvulsant drugs; carbamazepine, fosphenytoin, phenytoin, phenobarbitol, valproic acid. Folic acid may decrease a patient's response to methotrexate.

Vitamin D supplementation should not be given with large amounts of calcium in those with hypercalcemia or conditions that may lead to hypercalcemia such as hyperparathyroidism and those who form calcium-containing kidney stones.

Zinc can inhibit the absorption of certain antibiotics; taken at least 2 hours apart to minimize interactions.

Consult appropriate references for additional specific vitamin drug interactions.

Information for Patients:

Patients should be counseled to disclose all medical conditions, including use of all medications, vitamins and supplements, pregnancy, and breast-feeding.

Pediatric Use:

Not recommended for pediatric use.

ADVERSE REACTIONS:

Adverse reactions have been reported with specific vitamins and minerals, but generally at doses substantially higher than those
in Vitafol® One. However, allergic and idiosyncratic reactions are possible at any dose. Reported adverse events include skin ailments, gastrointestinal complaints, glucose abnormalities, and visual problems.

You should call your doctor for medical advice about serious adverse events. To report a serious adverse event or obtain product information, contact 1-877-324-9349.

DOSAGE AND ADMINISTRATION:

Before, during and after pregnancy, take one softgel capsule by mouth daily, or as directed by a physician.

HOW SUPPLIED:

Vitafol® One is available as dark a blue, oval shaped softgel capsule imprinted “EV0070”. Available in Box of Unit-Dose pack of 30 (5 child resistant blister cards of 6 softgel capsules), (0642-0070-30) and as professional samples (0642-0070-03).

STORAGE AND HANDLING

Store at room temperature, approximately 15°-30°C (59°-86°F), avoid excessive heat, light and moisture.

*These statements have not been evaluated by the Food and Drug Administration. This product is not intended to diagnose, treat, cure, or prevent any disease.

Rx

Distributed by:
Exeltis USA, Inc.
Florham Park, NJ 07932
1-877-324-9349
www.exeltisusa.com
©2025 Exeltis USA, Inc. All rights reserved.

U.S. Patent No. 8,183,227
Vitafol® is a trademark of Exeltis Healthcare S.L.
Rev. January 2025 0703001-05

PRINCIPAL DISPLAY PANEL - 30 Capsule Blister Pack Carton

0642-0070-30

VITAFOL
One

Prenatal Supplement with DHA

Unit Dose Pack
30 Softgel Capsules

RX
DIETARY SUPPLEMENT
U.S. PATENTED